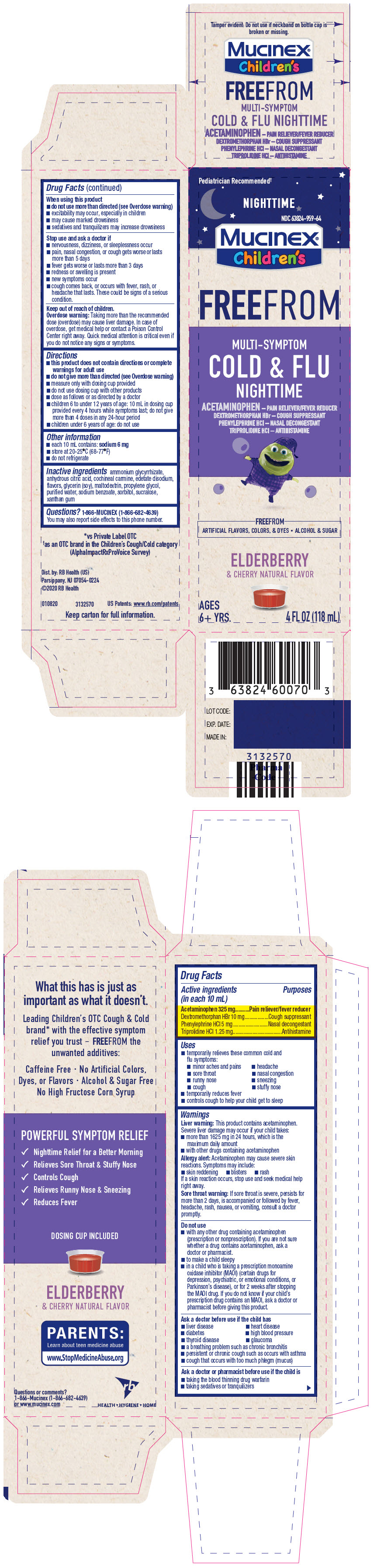 DRUG LABEL: Mucinex Childrens FreeFrom Multi-Symptom Cold and Flu Nighttime
NDC: 63824-959 | Form: SOLUTION
Manufacturer: RB Health (US) LLC
Category: otc | Type: HUMAN OTC DRUG LABEL
Date: 20241227

ACTIVE INGREDIENTS: ACETAMINOPHEN 325 mg/10 mL; DEXTROMETHORPHAN HYDROBROMIDE 10 mg/10 mL; PHENYLEPHRINE HYDROCHLORIDE 5 mg/10 mL; TRIPROLIDINE HYDROCHLORIDE 1.25 mg/10 mL
INACTIVE INGREDIENTS: AMMONIUM GLYCYRRHIZATE; ANHYDROUS CITRIC ACID; CARMINIC ACID; EDETATE DISODIUM; MALTODEXTRIN; PROPYLENE GLYCOL; WATER; SODIUM BENZOATE; SORBITOL; SUCRALOSE; XANTHAN GUM

Mucinex® Children's FreeFrom Multi-Symptom Cold & Flu Nighttime

Drug Facts

ACTIVE INGREDIENT

PURPOSE

Active ingredients (in each 10 mL) | Purposes
Acetaminophen 325 mg | Pain reliever/fever reducer
Dextromethorphan HBr 10 mg | Cough suppressant
Phenylephrine HCl 5 mg | Nasal decongestant
Triprolidine HCl 1.25 mg | Antihistamine

Uses

- temporarily relieves these common cold and flu symptoms:
  - minor aches and pains
  - headache
  - sore throat
  - nasal congestion
  - runny nose
  - sneezing
  - cough
  - stuffy nose
- temporarily reduces fever
- controls cough to help your child get to sleep

Warnings

Liver warning

This product contains acetaminophen. Severe liver damage may occur if your child takes:

- more than 1625 mg in 24 hours, which is the maximum daily amount
- with other drugs containing acetaminophen

Allergy alert

Acetaminophen may cause severe skin reactions. Symptoms may include:

- skin reddening
- blisters
- rash

If a skin reaction occurs, stop use and seek medical help right away.

Sore throat warning

If sore throat is severe, persists for more than 2 days, is accompanied or followed by fever, headache, rash, nausea, or vomiting, consult a doctor promptly.

Do not use

- with any other drug containing acetaminophen (prescription or nonprescription). If you are not sure whether a drug contains acetaminophen, ask a doctor or pharmacist.
- to make a child sleepy
- in a child who is taking a prescription monoamine oxidase inhibitor (MAOI) (certain drugs for depression, psychiatric, or emotional conditions, or Parkinson's disease), or for 2 weeks after stopping the MAOI drug. If you do not know if your child's prescription drug contains an MAOI, ask a doctor or pharmacist before giving this product.

Ask a doctor before use if the child has

- liver disease
- heart disease
- diabetes
- high blood pressure
- thyroid disease
- glaucoma
- a breathing problem such as chronic bronchitis
- persistent or chronic cough such as occurs with asthma
- cough that occurs with too much phlegm (mucus)

Ask a doctor or pharmacist before use if the child is

- taking the blood thinning drug warfarin
- taking sedatives or tranquilizers

When using this product

- do not use more than directed (see Overdose warning)
- excitability may occur, especially in children
- may cause marked drowsiness
- sedatives and tranquilizers may increase drowsiness

Stop use and ask a doctor if

- nervousness, dizziness, or sleeplessness occur
- pain, nasal congestion, or cough gets worse or lasts more than 5 days
- fever gets worse or lasts more than 3 days
- redness or swelling is present
- new symptoms occur
- cough comes back, or occurs with fever, rash, or headache that lasts. These could be signs of a serious condition.

Keep out of reach of children.

Overdose warning

Taking more than the recommended dose (overdose) may cause liver damage. In case of overdose, get medical help or contact a Poison Control Center right away. Quick medical attention is critical even if you do not notice any signs or symptoms.

Directions

- this product does not contain directions or complete warnings for adult use
- do not give more than directed (see Overdose warning)
- measure only with dosing cup provided
- do not use dosing cup with other products
- dose as follows or as directed by a doctor
- children 6 to under 12 years of age: 10 mL in dosing cup provided every 4 hours while symptoms last; do not give more than 4 doses in any 24-hour period
- children under 6 years of age: do not use

Other information

- each 10 mL contains: sodium 6 mg
- store at 20-25°C (68-77°F)
- do not refrigerate

Inactive ingredients

ammonium glycyrrhizate, anhydrous citric acid, cochineal carmine, edetate disodium, flavors, glycerin (soy), maltodextrin, propylene glycol, purified water, sodium benzoate, sorbitol, sucralose, xanthan gum

Questions?

1-866-MUCINEX (1-866-682-4639)

You may also report side effects to this phone number.

Dist. by: RB Health (US)
Parsippany, NJ 07054-0224

PRINCIPAL DISPLAY PANEL - 118 mL Bottle Carton

Pediatrician Recommended†

NIGHTTIME

NDC 63824-959-64

Mucinex®
Children's

FREEFROM

MULTI-SYMPTOM
COLD & FLU
NIGHTTIME

ACETAMINOPHEN – PAIN RELIEVER/FEVER REDUCER
DEXTROMETHORPHAN HBr – COUGH SUPPRESSANT
PHENYLEPHRINE HCl – NASAL DECONGESTANT
TRIPROLIDINE HCl – ANTIHISTAMINE

FREEFROM
ARTIFICIAL FLAVORS, COLORS, & DYES • ALCOHOL & SUGAR

ELDERBERRY
& CHERRY NATURAL FLAVOR

AGES
6+ YRS.

4 FL OZ (118 mL)